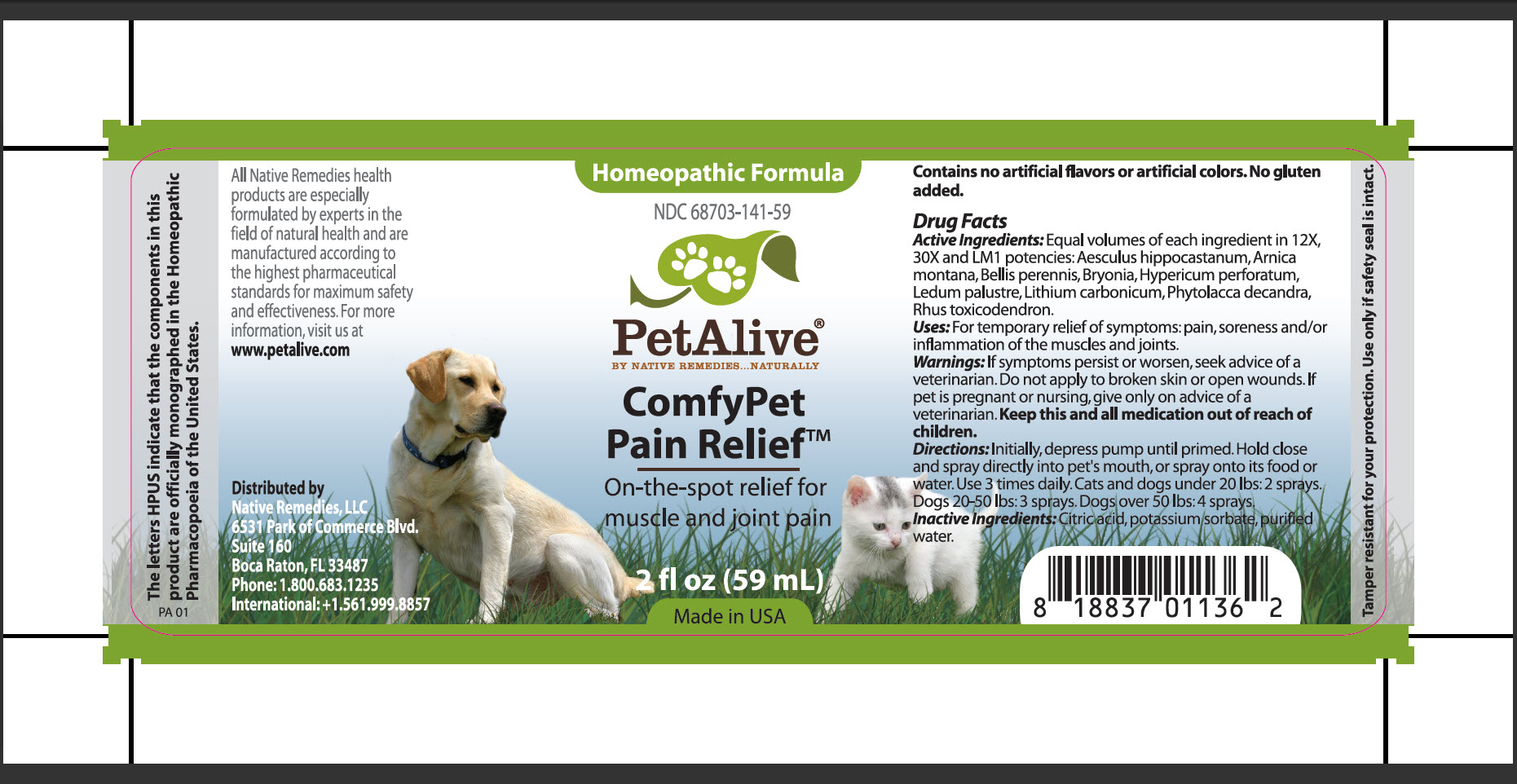 DRUG LABEL: ComfyPet Pain Relief
NDC: 68703-141 | Form: SPRAY
Manufacturer: SILVER STAR BRANDS
Category: homeopathic | Type: OTC ANIMAL DRUG LABEL
Date: 20251118

ACTIVE INGREDIENTS: HORSE CHESTNUT 12 [hp_X]/59 mL; ARNICA MONTANA 12 [hp_X]/59 mL; BELLIS PERENNIS 12 [hp_X]/59 mL; BRYONIA ALBA ROOT 12 [hp_X]/59 mL; HYPERICUM PERFORATUM 12 [hp_X]/59 mL; LEDUM PALUSTRE TWIG 12 [hp_X]/59 mL; LITHIUM CARBONATE 12 [hp_X]/59 mL; PHYTOLACCA AMERICANA ROOT 12 [hp_X]/59 mL; TOXICODENDRON PUBESCENS LEAF  12 [hp_X]/59 mL
INACTIVE INGREDIENTS: CITRIC ACID MONOHYDRATE; POTASSIUM SORBATE; WATER

ConfyPet Pain Relief

PURPOSE

On-the-spot relief for muscle and joint pain

Drug Facts
Active Ingredients: Equal volumes of each ingredient in 12X, 30X and LM! potencies: Aesculus hippocastanum, Arnica montana, Bellis pereniss, Bryonia, Hypericum perforatum, Ledum palustre, Lithium carbonicum, Phytolacca decandra, Rhus toxicodendron

INDICATIONS AND USAGE

Uses:For temporary relief of symptoms: pain, soreness and/or inflammation of the muscles and joints

WARNINGS

Warnings: If symptoms persist or worsen, seek advice of a veterinarian. Do not apply to broken skin or open wounds.

PREGNANCY OR BREAST FEEDING

If pet is pregnant or nursing, give only on advice of a veterinarian

KEEP OUT OF REACH OF CHILDREN

Keep this and all medication out of reach of children

DOSAGE AND ADMINISTRATION

Directions:Initially, depress pump until primed. Hold close and spray directly into pet's mouth, or spray onto its food or water. Use 3 times daily. Cats and dogs under 20 lbs: 2 sprays. Dogs 20-50 lbs: 3 sprays. Dogs over 50 lbs: 4 sprays

Inactive Ingredients:Citric acid, potassium sorbate, purified water

INFORMATION FOR OWNERS/CAREGIVERS

The letters HPUS indicate that the components in this product are officially monographed in the Homeopathic Pharmacopoeia of the United States

All Native Remedies health products are especially formulated by experts in the field of natural health and are manufactured according to the highest pharmaceutical standards for maximum safety and effectiveness. For more information, visit us at www.petalive.com

Distributed by
Native Remedies, LLC
6531 Park of Commerce Blvd.
Suite 160
Boca Raton, FL 33487
Phone: 1.800.683.1235
International: +1.561.999.8857

Contains no artificial flavors or artificial colors. No gluten added

STORAGE AND HANDLING

Tamper resistant for your protection. Use only if safety seal is intact